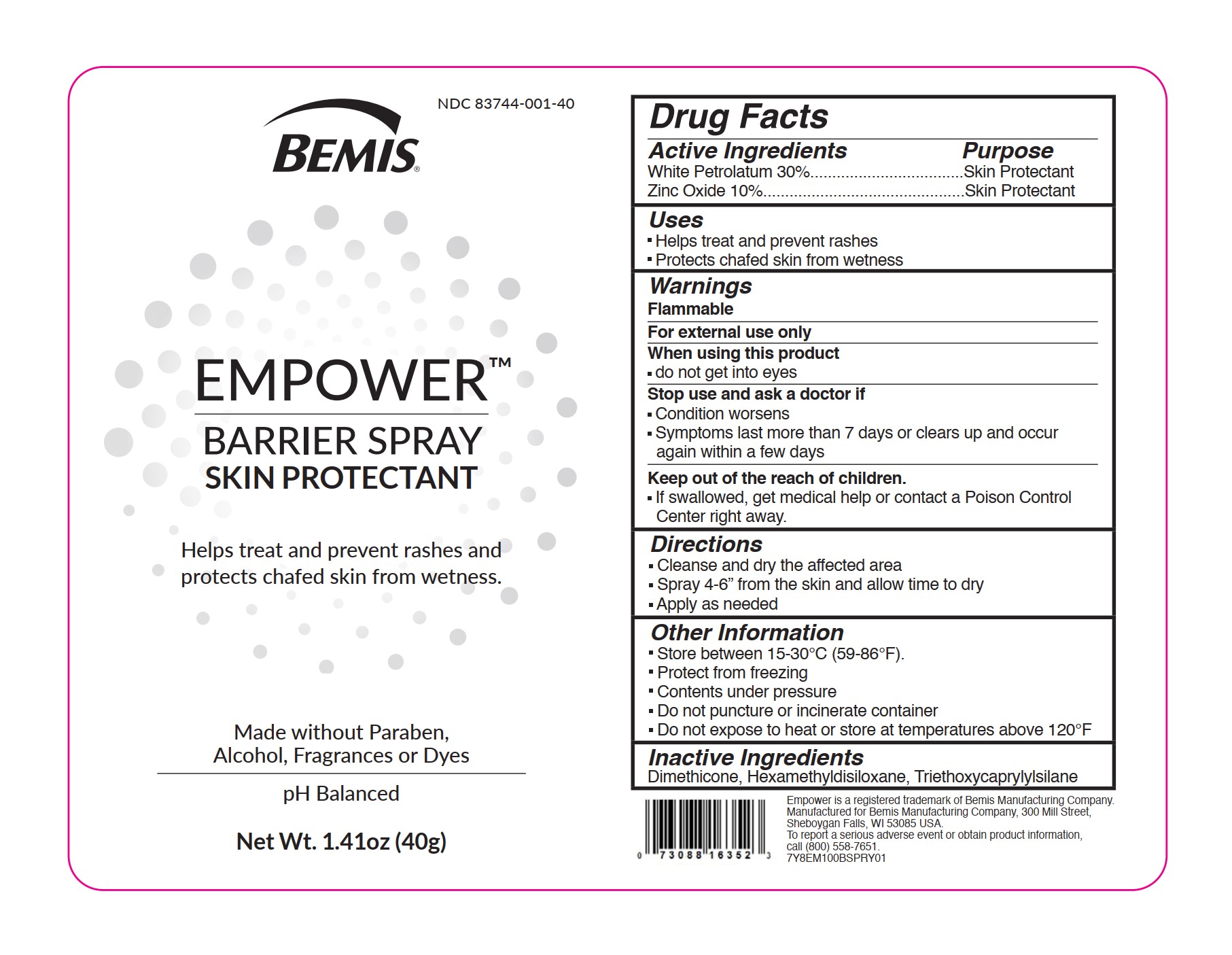 DRUG LABEL: Empower
NDC: 83744-001 | Form: SPRAY
Manufacturer: Bemis Manufacturing Company Inc
Category: otc | Type: HUMAN OTC DRUG LABEL
Date: 20231018

ACTIVE INGREDIENTS: WHITE PETROLATUM 30 g/100 g; ZINC OXIDE 10 g/100 g
INACTIVE INGREDIENTS: HEXAMETHYLDISILOXANE; DIMETHICONE; TRIETHOXYCAPRYLYLSILANE

Empower

Active ingredients

White Petrolatum 30%

Zinc Oxide 10%

Purpose

White Petrolatum 30%.................Skin Protectant

Zinc Oxide 10%...........................Skin Protectant

Uses

- Helps treat and prevent rashes
- Protects chafed skin from wetness

Warnings

Flammable

For external use only

When using this product

- Do not get into eyes

Stop use and ask a doctor if

- Condition worsens
- Symptoms last more than 7 days or clears up and occur again within a few days

Keep out of the reach of children.

- If swallowed, get medical help or contact a Poison Control Center right away.

Directions

- Cleanse and dry the affected area
- Spray 4-6" from the skin and allow time to dry
- Apply as needed

Other Information

- Store between 15-30C (59-86F)
- Protect from freezing
- Contents under pressure
- Do not puncture or incinerate container
- Do not expose to heat or store at temperatures above 120F

Inactive Ingredients

Dimethicone, Hexamethyldisiloxane, Triethoxycaprylylsilane

PACKAGE LABEL

BEMIS

NDC 83744-001-40

EMPOWER

BARRIER SPRAY

SKIN PROTECTANT

Helps treat and prevent rashes and protects chafed skin from wetness.

Made without Paraben, Alcohol, Fragrances or Dyes

pH Balanced

Net Wt. 1.41oz (40g)